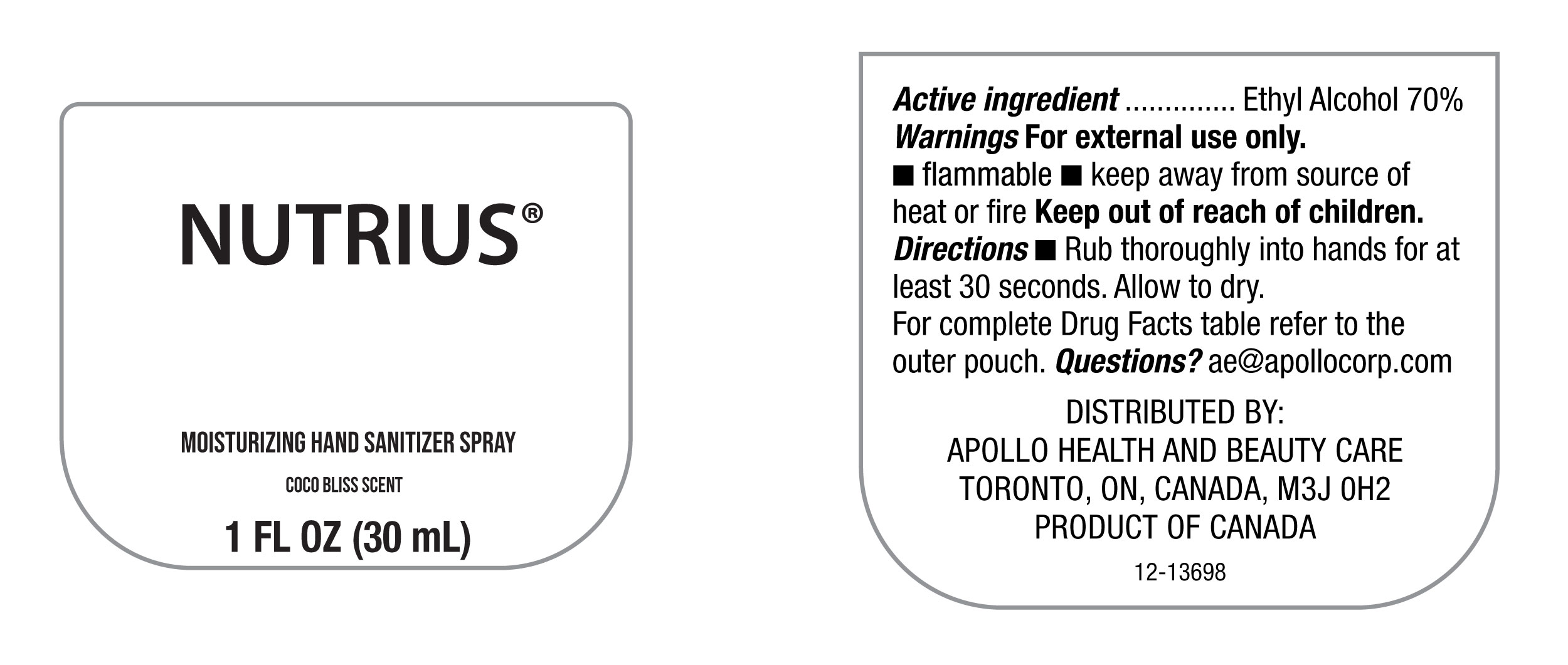 DRUG LABEL: Hand Sanitizer
NDC: 63148-122 | Form: SPRAY
Manufacturer: Apollo Health and Beauty Care
Category: otc | Type: HUMAN OTC DRUG LABEL
Date: 20260114

ACTIVE INGREDIENTS: ALCOHOL 70 mL/100 mL
INACTIVE INGREDIENTS: FRAGRANCE CLEAN ORC0600327; ISOPROPYL MYRISTATE; ORANGE 4; ALOE BARBADENSIS LEAF POWDER; WATER; .ALPHA.-TOCOPHEROL ACETATE, D-; TRIS(TETRAMETHYLHYDROXYPIPERIDINOL) CITRATE; ISOPROPYL ALCOHOL; GLYCERIN; YELLOW 5

NDC-63148-122, Nutrius Moisturizing Hand Sanitizer Spray

Active Ingredient

Ethyl Alcohol 70%

Purpose

Antiseptic

Uses

For Personal Hygiene to help prevent the spread of bacteria and can be used in place of hand washing if soap and water are not available.

Warnings

For external use only

- Flammable
- Keep away from source of heat or fire.

Do not use

- on infants less than 2 months of age.
- On open skin wounds.
- on broken or damaged skin.

When using this product avoid

- Contact with eyes. If contact occurs, rinse eyes throughly with water.
- Do not inhale.

Stop use and ask a doctor.

If irritation or redness develops and lasts.

Keep out of reach of children.

In case of accidental ingestion, get medical help or contact a Poison Control Center immediately.

Directions

- For Occassional and Personal use.
- Rub thoroughly into hands for at least 30 seconds.Allow to dry.
- Children under 6 years should be supervised when using the product..

Inactive Ingredients

Aloe Barbadensis Leaf Powder, Fragrance (Parfum), Glycerin, Isopropyl Alcohol, Isopropyl Myristate, Orange 4 (CI 15510), Tocopheryl Acetate, Tris(Tetramethylhydroxypiperidinol) Citrate, Water (Aqua), Yellow 5 (Cl 19140).

Questions?

ae@apollocorp.com